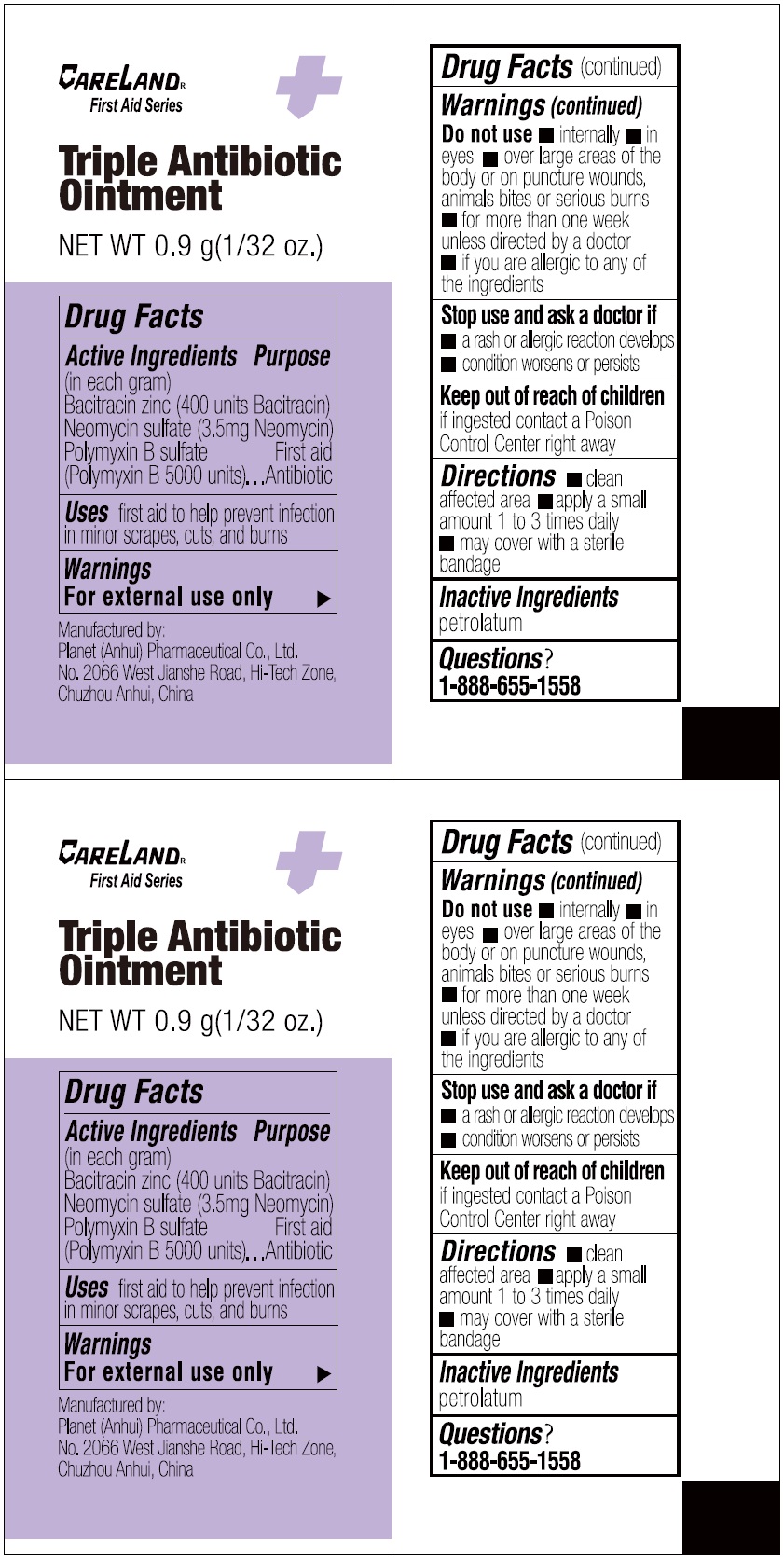 DRUG LABEL: Careland Triple Antibiotic
NDC: 75568-015 | Form: OINTMENT
Manufacturer: Planet (Anhui) Pharmaceutical Co., Ltd.
Category: otc | Type: HUMAN OTC DRUG LABEL
Date: 20231109

ACTIVE INGREDIENTS: BACITRACIN ZINC 400 [CFU]/1 g; NEOMYCIN SULFATE 3.5 mg/1 g; POLYMYXIN B SULFATE 5000 [CFU]/1 g
INACTIVE INGREDIENTS: PETROLATUM

Careland Triple Antibiotic Ointment

Active Ingredients

(in each gram) Bacitracin zinc (400 units Bacitracin) Neomycin sulfate (3.5mg Neomycin) Polymyxin B sulfate (Polymyxin B 5000 units)

Purpose

First aid Antibiotic

Uses

first aid to help prevent infection in minor scrapes, cuts, and burns

Warnings

For external use only

Do not use

• internally • in eyes • over large areas of the body or on puncture wounds, animals bites or serious burns • for more than one week unless directed by a doctor • if you are allergic to any of the ingredients

Stop use and ask a doctor if

• a rash or allergic reaction develops

• condition worsens or persists

Keep out of reach of children

if ingested contact a Poison Control Center right away

Directions

• clean affected area • apply a small amount 1 to 3 times daily • may cover with a sterile bandage

Inactive Ingredients

petrolatum

Questions?

1-888-655-1558